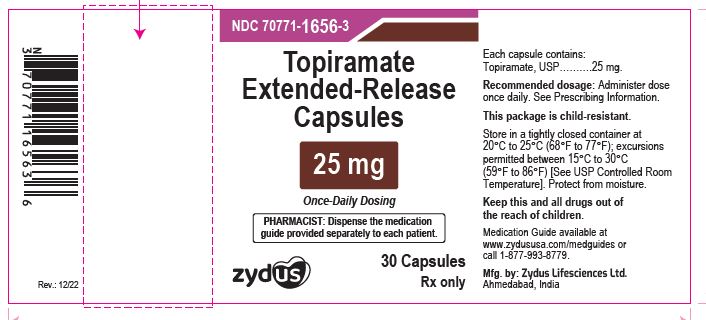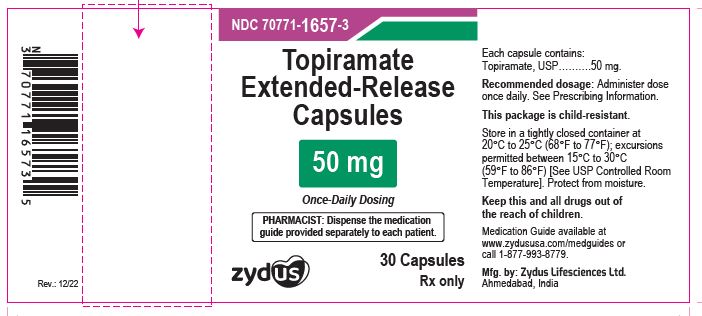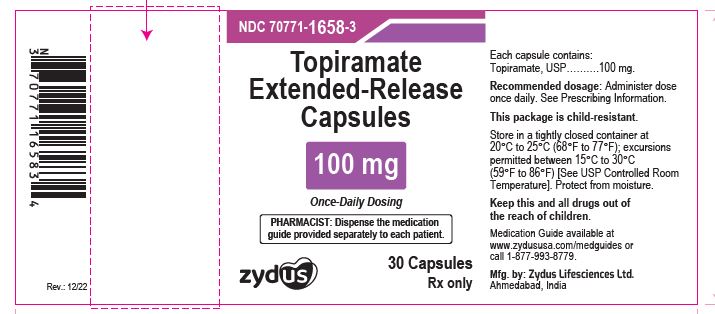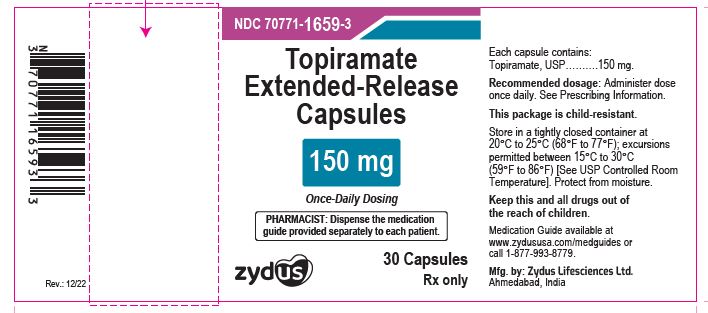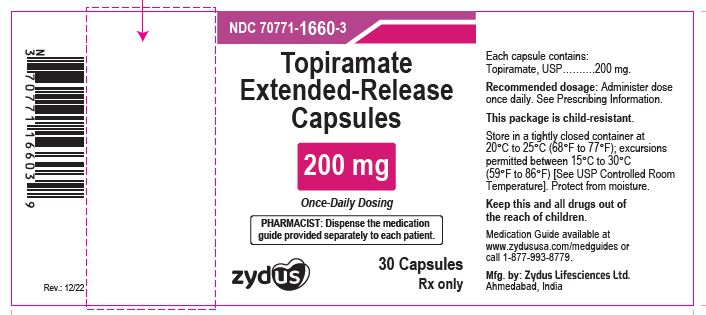 DRUG LABEL: Topiramate
NDC: 70771-1656 | Form: CAPSULE, EXTENDED RELEASE
Manufacturer: Zydus Lifesciences Limited
Category: prescription | Type: HUMAN PRESCRIPTION DRUG LABEL
Date: 20230928

ACTIVE INGREDIENTS: TOPIRAMATE 25 mg/1 1
INACTIVE INGREDIENTS: ETHYLCELLULOSE (10 MPA.S); ETHYLCELLULOSE (45 MPA.S); FERRIC OXIDE RED; FERROSOFERRIC OXIDE; HYDROXYPROPYL CELLULOSE, LOW SUBSTITUTED; HYPROMELLOSE 2910 (15 MPA.S); HYPROMELLOSE 2910 (6 MPA.S); MICROCRYSTALLINE CELLULOSE; POLYETHYLENE GLYCOL 3350; POLYETHYLENE GLYCOL 400; POTASSIUM HYDROXIDE; PROPYLENE GLYCOL; SHELLAC; TALC; TITANIUM DIOXIDE; TRIETHYL CITRATE; WATER

TOPIRAMATE extended-release capsules, for oral use

PACKAGE LABEL.PRINCIPAL DISPLAY PANEL

NDC 70771-1656-3

Topiramate extended-release Capsules 25 mg

Rx only

30 Capsules

NDC 70771-1657-3

Topiramate extended-release Capsules 50 mg

Rx only

30 Capsules

NDC 70771-1658-3

Topiramate extended-release Capsules 100 mg

Rx only

30 Capsules

NDC 70771-1659-3

Topiramate extended-release Capsules 150 mg

Rx only

30 Capsules

NDC 70771-1660-3

Topiramate extended-release Capsules 200 mg

Rx only

30 Capsules